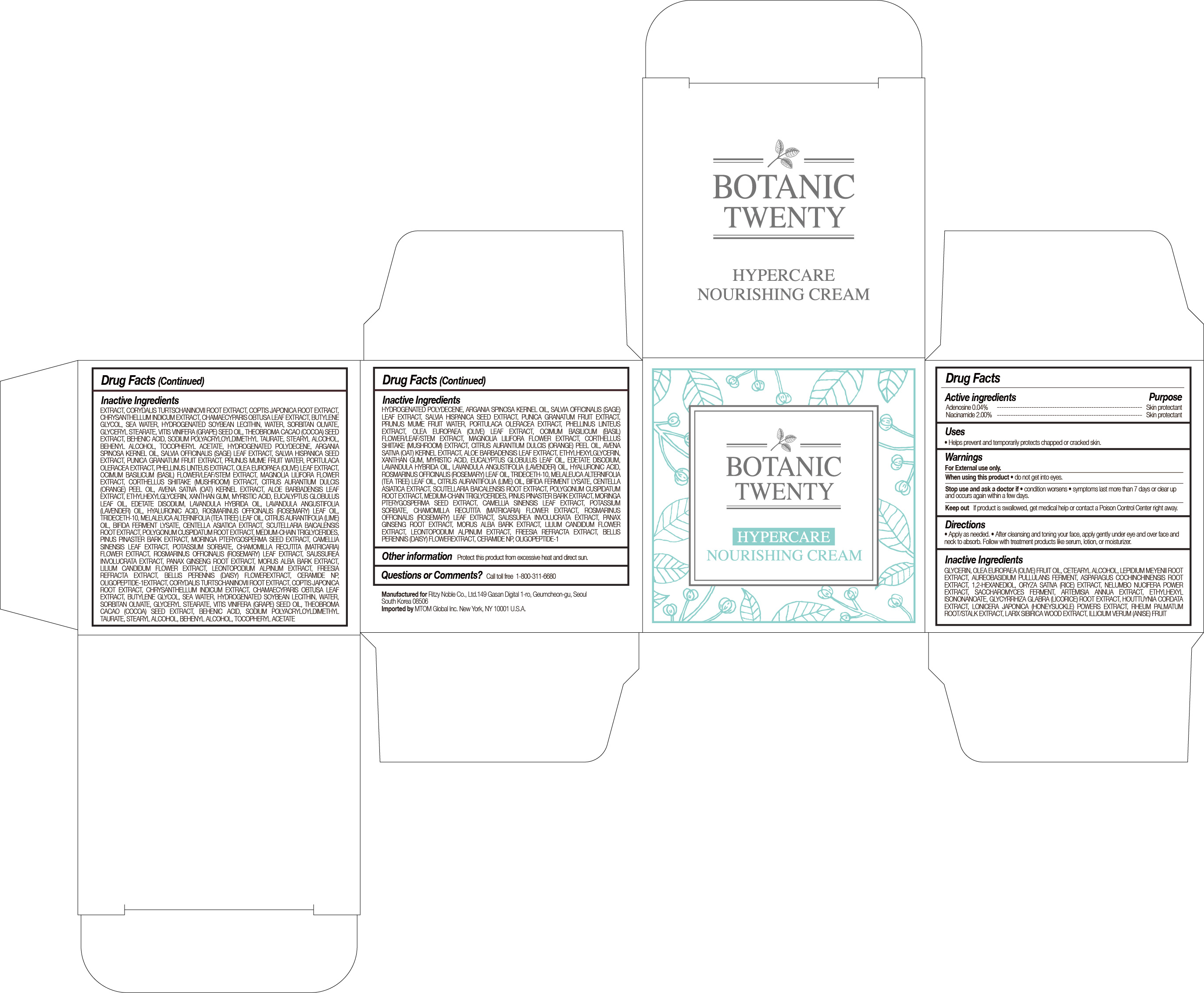 DRUG LABEL: BOTANIC TWENTY
NDC: 71364-102 | Form: CREAM
Manufacturer: RITZY NOBLE CO., LTD.
Category: otc | Type: HUMAN OTC DRUG LABEL
Date: 20180101

ACTIVE INGREDIENTS: ADENOSINE 0.04 g/150 mL; NIACINAMIDE 2 g/150 mL
INACTIVE INGREDIENTS: SORBITAN OLIVATE; .ALPHA.-TOCOPHEROL ACETATE; THEOBROMA CACAO WHOLE; BEHENIC ACID; HYDROGENATED SOYBEAN LECITHIN; BETAINE; 1,2-HEXANEDIOL; DIPROPYLENE GLYCOL; NELUMBO NUCIFERA FLOWER; ARTEMISIA ANNUA WHOLE; SACCHAROMYCES LYSATE; ARGININE; COPTIS JAPONICA ROOT; CHAMAECYPARIS OBTUSA LEAF; RHEUM PALMATUM ROOT; BUTYLENE GLYCOL; LEPIDIUM MEYENII ROOT; AUREOBASIDIUM PULLULANS VAR. PULLUTANS; WATER; GLYCERIN; LONICERA JAPONICA FLOWER; CHRYSANTHEMUM INDICUM FLOWER; CORYDALIS TURTSCHANINOVII WHOLE; ILLICIUM VERUM WHOLE; LARIX SIBIRICA WOOD; ETHYLHEXYLGLYCERIN; CITRUS AURANTIUM FRUIT OIL; CENTELLA ASIATICA; EUCALYPTUS GLOBULUS LEAF; LAVANDULA ANGUSTIFOLIA FLOWER; PINUS PINASTER WOOD; SCUTELLARIA BAICALENSIS ROOT; ROSMARINUS OFFICINALIS FLOWERING TOP OIL; MELALEUCA ALTERNIFOLIA LEAF; ROSMARINUS OFFICINALIS WHOLE; BELLIS PERENNIS FLOWER; FREESIA ALBA FLOWER; LEONTOPODIUM ALPINUM; LILIUM CANDIDUM FLOWER; MORUS ALBA BARK; PANAX GINSENG ROOT WATER; MAGNOLIA LILIIFLORA FLOWER; PUNICA GRANATUM SEED; EDETATE DISODIUM; SAUSSUREA INVOLUCRATA FLOWERING TOP; ASPARAGUS COCHINCHINENSIS WHOLE; HOUTTUYNIA CORDATA TOP; ORYZA SATIVA WHOLE; ALOE VERA LEAF; GLYCYRRHIZA GLABRA; POLYSORBATE 80; ALLANTOIN; OLEA EUROPAEA FRUIT VOLATILE OIL; GLYCERYL MONOSTEARATE; ARGANIA SPINOSA SEED; PRUNUS MUME FRUIT OIL; VITIS VINIFERA SEED; STEARYL ALCOHOL; SALVIA OFFICINALIS FLOWERING TOP; SALVIA HISPANICA SEED; CETOSTEARYL ALCOHOL; ETHYLHEXYL ISONONANOATE

Botanic Twenty Hypercare Nourishing Cream

BOTANIC TWENTY HYPERCARE NOURISHING CREAM

ACTIVE INGREDIENTS

ADENOSINE 0.04%

NIACINAMIDE 2.00%

PURPOSE

SKIN PROTECTANT

USES

Helps prevent and temporarily protects chapped or cracked skin.

WARNINGS

FOR EXTERNAL USE ONLY

WHEN USING THIS PRODUCT

• do not get into eyes.

STOP USE AND ASK A DOCTOR IF

• condition worsens

• symptoms last more than 7 days or clear up and occurs again within a few days.

KEEP OUT OF REACH OF CHILDREN

If product is swallowed, get medical help or contact a Poison Control Center right away.

DIRECTIONS

• Apply as needed.

• After cleansing and toning your face, apply gently under eye and over face and neck to absorb. Follow with treatment products like serum, lotion, or moisturizer.

INACTIVE INGREDIENTS

GLYCERIN, OLEA EUROPAEA (OLIVE) FRUIT OIL, CETEARYL ALCOHOL, LEPIDIUM MEYENII ROOT EXTRACT, AUREOBASIDIUM PULLULANS FERMENT, ASPARAGUS COCHINCHINENSIS ROOT EXTRACT, 1,2-HEXANEDIOL, ORYZA SATIVA (RICE) EXTRACT, NELUMBO NUCIFERA FLOWER EXTRACT, SACCHAROMYCES FERMENT, ARTEMISIA ANNUA EXTRACT, ETHYLHEXYL ISONONANOATE, GLYCYRRHIZA GLABRA (LICORICE) ROOT EXTRACT, HOUTTUYNIA CORDATA EXTRACT, LONICERA JAPONICA (HONEYSUCKLE) FLOWER EXTRACT, RHEUM PALMATUM ROOT/STALK EXTRACT, LARIX SIBIRICA WOOD EXTRACT, ILLICIUM VERUM (ANISE) FRUIT EXTRACT, CORYDALIS TURTSCHANINOVII ROOT EXTRACT, COPTIS JAPONICA ROOT EXTRACT, CHRYSANTHELLUM INDICUM EXTRACT, CHAMAECYPARIS OBTUSA LEAF EXTRACT, BUTYLENE GLYCOL, SEA WATER, NIACINAMIDE, BUTYROSPERMUM PARKII (SHEA) BUTTER, MACADAMIA TERNIFOLIA SEED OIL, STEARIC ACID, CETEARYL OLIVATE, HYDROGENATED LECITHIN, WATER, SORBITAN OLIVATE, GLYCERYL STEARATE, VITIS VINIFERA (GRAPE) SEED OIL, THEOBROMA CACAO (COCOA) SEED EXTRACT, BEHENIC ACID, SODIUM POLYACRYLOYLDIMETHYL TAURATE, STEARYL ALCOHOL, BEHENYL ALCOHOL, TOCOPHERYL ACETATE, HYDROGENATED POLYDECENE, ARGANIA SPINOSA KERNEL OIL, SALVIA OFFICINALIS (SAGE) LEAF EXTRACT(0.9%), SALVIA HISPANICA SEED EXTRACT, PUNICA GRANATUM FRUIT EXTRACT, PRUNUS MUME FRUIT WATER, PORTULACA OLERACEA EXTRACT, PHELLINUS LINTEUS EXTRACT, OLEA EUROPAEA (OLIVE) LEAF EXTRACT, OCIMUM BASILICUM (BASIL) FLOWER/LEAF/STEM EXTRACT, MAGNOLIA LILIFLORA FLOWER EXTRACT, CORTHELLUS SHIITAKE (MUSHROOM) EXTRACT, CITRUS AURANTIUM DULCIS (ORANGE) PEEL OIL, AVENA SATIVA (OAT) KERNEL EXTRACT, ALOE BARBADENSIS LEAF EXTRACT, ETHYLHEXYLGLYCERIN, XANTHAN GUM, ADENOSINE, MYRISTIC ACID, EUCALYPTUS GLOBULUS LEAF OIL, DISODIUM EDTA, LAVANDULA HYBRIDA OIL, LAVANDULA ANGUSTIFOLIA (LAVENDER) OIL, HYALURONIC ACID, ROSMARINUS OFFICINALIS (ROSEMARY) LEAF OIL, TRIDECETH-10, MELALEUCA ALTERNIFOLIA (TEA TREE) LEAF OIL, CITRUS AURANTIFOLIA (LIME) OIL, BIFIDA FERMENT LYSATE, CENTELLA ASIATICA EXTRACT, SCUTELLARIA BAICALENSIS ROOT EXTRACT, POLYGONUM CUSPIDATUM ROOT EXTRACT, CAPRYLIC/CAPRIC TRIGLYCERIDE, PINUS PINASTER BARK EXTRACT, MORINGA PTERYGOSPERMA SEED EXTRACT, CAMELLIA SINENSIS LEAF EXTRACT, POTASSIUM SORBATE, CHAMOMILLA RECUTITA (MATRICARIA) FLOWER EXTRACT, ROSMARINUS OFFICINALIS (ROSEMARY) LEAF EXTRACT, SAUSSUREA INVOLUCRATA EXTRACT, PANAX GINSENG ROOT EXTRACT, MORUS ALBA BARK EXTRACT, LILIUM CANDIDUM FLOWER EXTRACT, LEONTOPODIUM ALPINUM EXTRACT, FREESIA REFRACTA EXTRACT, BELLIS PERENNIS (DAISY) FLOWER EXTRACT, CERAMIDE NP, OLIGOPEPTIDE-1

OTHER INFORMATION

Protect this product from excessive heat and direct sun.

QUESTIONS OR COMMENTS?

Call toll free 1-800-311-6680